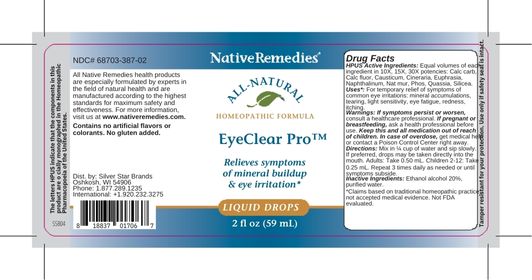 DRUG LABEL: EyeClear Pro
NDC: 68703-387 | Form: LIQUID
Manufacturer: Silver Star Brands
Category: homeopathic | Type: HUMAN OTC DRUG LABEL
Date: 20230216

ACTIVE INGREDIENTS: NAPHTHALENE 30 [hp_X]/59 mL; CAUSTICUM 30 [hp_X]/59 mL; CALCIUM FLUORIDE 30 [hp_X]/59 mL; SENECIO VULGARIS 30 [hp_X]/59 mL; OYSTER SHELL CALCIUM CARBONATE, CRUDE 30 [hp_X]/59 mL; SILICON DIOXIDE 30 [hp_X]/59 mL; SODIUM CHLORIDE 30 [hp_X]/59 mL; PHOSPHORUS 30 [hp_X]/59 mL; EUPHRASIA STRICTA 30 [hp_X]/59 mL; QUASSIA AMARA WOOD 30 [hp_X]/59 mL
INACTIVE INGREDIENTS: ALCOHOL; WATER

NativeRemedies® EyeClear Pro™

HPUS Active Ingredients: Equal volumes of each ingredient in 10X, 15X, 30X potencies: Calc carb, Calc fluor, Causticum, Cineraria, Euphrasia, Naphthalinum, Nat mur, Phos, Quassia, Silicea.

The letters UPUS indicate that the components in this product are officially monographed in the Homeopathic Pharmacopoeia of the United States.

Uses*

Uses*: For temporary relief of symptoms of common eye irritations: mineral accumulations, tearing, light sensitivity, eye fatigue, redness, itching.

*Claims based on traditional homeopathic practice, not accepted medical evidence. Not FDA evaluated.

Warnings

If symptoms persist or worsen, consult a healthcare professional. If pregnant or breastfeeding, ask a health professional before use. Keep this and all medication out of reach of children. In case of overdose, get medical help or contact a Poison Control Center right away.

Directions

Directions: Mix in 1/4 cup water and sip slowly. If preferred, drops may be taken directly into the mouth. Adults: Take 0.50 mL. Children 2-12: Take 0.20 mL. Repeat 3 times daily as needed or until symptoms subside.

OTHER SAFETY INFORMATION

Contains no artificial flavors or colorants. No gluten added.

Tamper resistant for your protection. Use only if safety seal is intact.

Inactive Ingredients

Inacitve Ingredients: Ethanol alcohol 20%, purified water.

KEEP OUT OF REACH OF CHILDREN

Keep this and all medications out of reach of children.

PREGNANCY OR BREAST FEEDING

If pregnant or breastfeeding, ask a health professional before use.

PURPOSE

Relieves symptoms of mineral buildup & eye irritation.